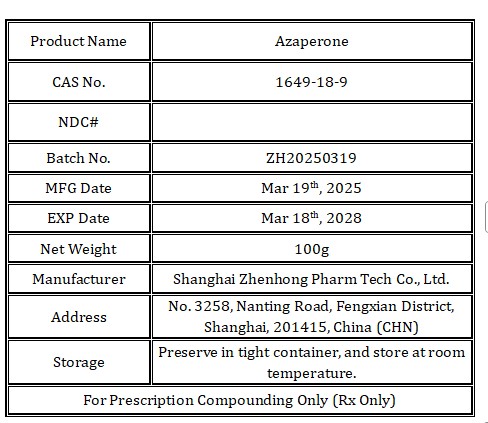 DRUG LABEL: Azaperone
NDC: 86228-112 | Form: POWDER
Manufacturer: Shanghai Zhenhong Pharm Tech Co., Ltd.
Category: other | Type: BULK INGREDIENT - ANIMAL DRUG
Date: 20250625

ACTIVE INGREDIENTS: Azaperone 1 kg/1 kg

Azaperone